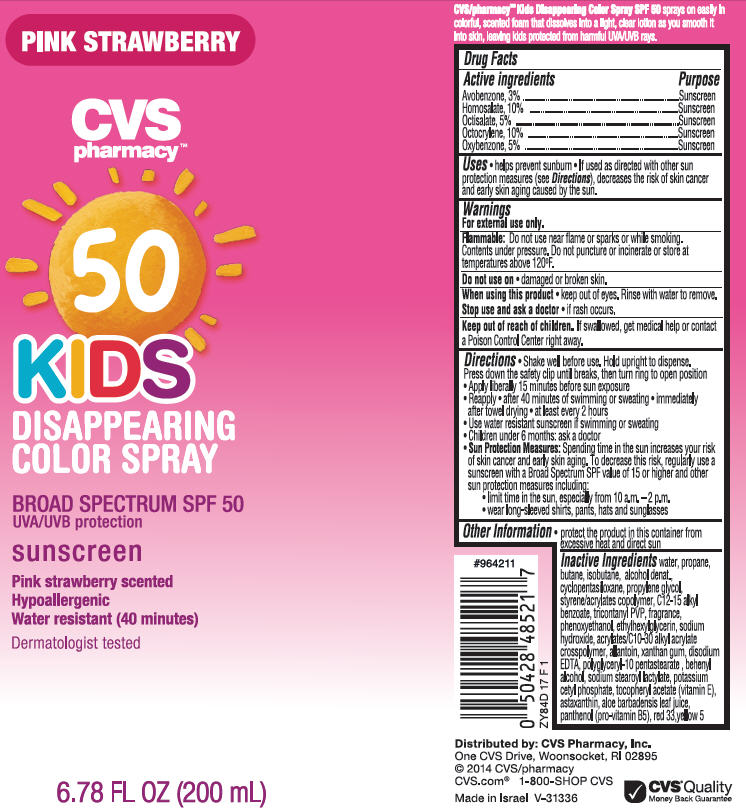 DRUG LABEL: Kids Disappearing Color SPF50 Broad Spectrum Suncreen Pink Strawberry Scented
NDC: 59779-624 | Form: SPRAY
Manufacturer: CVS Pharmacy
Category: otc | Type: HUMAN OTC DRUG LABEL
Date: 20140121

ACTIVE INGREDIENTS: AVOBENZONE 3 g/100 mL; HOMOSALATE 10 g/100 mL; OCTISALATE 5 g/100 mL; OCTOCRYLENE 10 g/100 mL; OXYBENZONE 5 g/100 mL
INACTIVE INGREDIENTS: WATER; PROPANE; BUTANE; ISOBUTANE; ALCOHOL; CYCLOMETHICONE 5; PROPYLENE GLYCOL; STYRENE; ALKYL (C12-15) BENZOATE; TRICONTANYL POVIDONE (4 TRICONTANYL BRANCHES/REPEAT); PHENOXYETHANOL; ETHYLHEXYLGLYCERIN; SODIUM HYDROXIDE; CARBOMER INTERPOLYMER TYPE A (ALLYL SUCROSE CROSSLINKED); ALLANTOIN; XANTHAN GUM; EDETATE DISODIUM; POLYGLYCERYL-10 STEARATE; DOCOSANOL; SODIUM STEAROYL LACTYLATE; POTASSIUM CETYL PHOSPHATE; .ALPHA.-TOCOPHEROL ACETATE; ASTAXANTHIN; ALOE VERA LEAF; PANTHENOL; D&C RED NO. 33; FD&C YELLOW NO. 5

PINK STRAWBERRY CVS pharmacy™ KIDS Disappearing Color Spray
Broad Spectrum SPF 50 UVA/UVB protection Sunscreen

Active ingredient

Avobenzone, 3%
Homosalate, 10%
Oclisalate 5%
Octocrylene 10%
Oxybenzone, 5%

Purpose

Sunscreen

Uses

- helps prevent sunburn
- If used as directed with other sun protection measures (see Directions), decreases the risk of skin cancer and early skin aging caused by the sun

Warnings

For external use only.

Flammable

Do not use near flame or sparks or while smoking. Contents under pressure. Do not puncture or incinerate or store at temperatures above 120°F.

Do not use on

- damaged or broken skin.

When using this product

- keep out of eyes. Rinse with water to remove.

Stop use and ask a doctor

- if rash occurs.

Keep Out of Reach of Children.

If swallowed, get medical help or contact a Poison Control Center right away.

Directions

- Shake well before use. Hold upright to dispense. Press down the safety clip until breaks, then turn ring to open position
- Apply liberally 15 minutes before sun exposure.
- Reapply
  - after 40 minutes of swimming or sweating
  - immediately after towel drying
  - at least every 2 hours
- Use water-resistant sunscreen if swimming or sweating
- Children under 6 months: ask a doctor
- Sun Protection Measures: Spending time in the sun increases your risk of skin cancer and early skin aging. To decrease this risk, regularly use a sunscreen with a Broad Spectrum SPF value of 15 or higher and other sun protection measures including:
  - limit time in the sun, especially from 10 a.m. - 2 p.m.
  - wear long-sleeved shirts, pants, hats and sunglasses

Other Information

- protect the product in this container from excessive heat and direct sun

Inactive Ingredients

water, propane, butane, isobutene, alcohol denat., cyclopentasiloxane, propylene glycol, styrene/acrylates copolymer, C12-15 alkyl benzoate, tricontanyl PVP, fragrance, phenoxyethanol, ethylhexylglycerin, sodium hydroxide, acrylates/C10-30 alkyl acrylate crosspolymer, allantoin, xanthan gum, disodium EDTA, polyglyceryl-10 pentastearate, behenyl alcohol, sodium stearoyl lactylate, potassium cetyl phosphate, tocopheryl acetate (vitamin E), astaxanthin, aloe barbadensis leaf juice, panthenol (pro-vitamin B5), red 33, yellow 5

Package/Label Principal Display Panel - Carton Label

PINK STRAWBERRY
CVS pharmacy™
KIDS DISAPEARING COLOR SPRAY
BROAD SPECTRUM SPF 50
UVA/UVB protection
SUNSCREEN
Pink strawberry scented
Hypoallergenic
Water resistant (40 minutes)
Dermatologist tested
6.78 FL OZ (200 mL)

CVS/pharmacy™ Kids Disappearing Color Spray SPF 50 sprays on easily in colorful, scented foam that dissolves into a light, clear lotion as you smooth it into skin, leaving kids protected from harmful UVA/UVB rays.

Carton Label